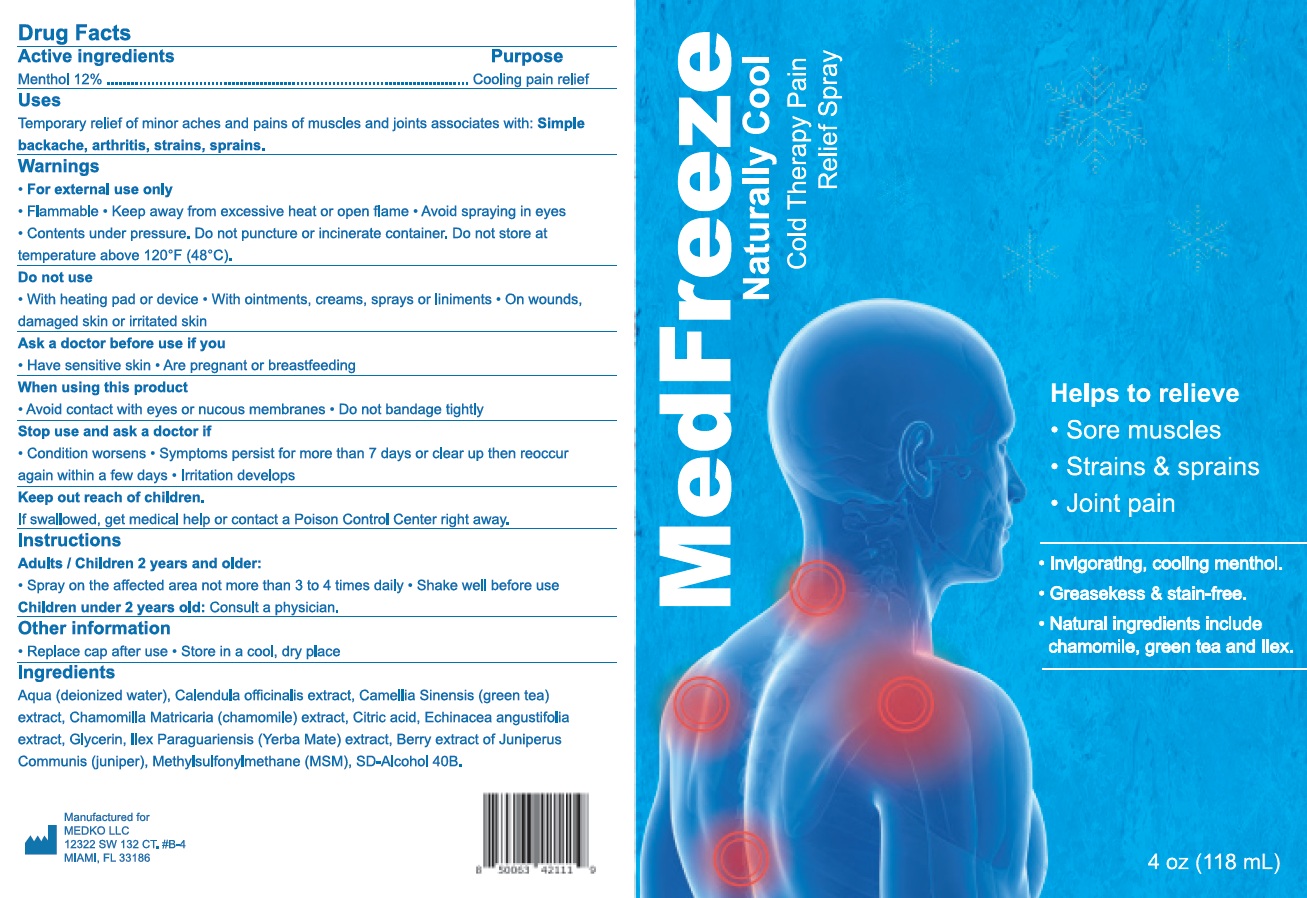 DRUG LABEL: MedFreeze Naturally Cool Pain Relief
NDC: 84443-487 | Form: LIQUID
Manufacturer: MEDKO LLC
Category: otc | Type: HUMAN OTC DRUG LABEL
Date: 20250915

ACTIVE INGREDIENTS: MENTHOL 120 mg/1 mL
INACTIVE INGREDIENTS: WATER; CALENDULA OFFICINALIS FLOWER; GREEN TEA LEAF; CHAMOMILE; CITRIC ACID MONOHYDRATE; ECHINACEA ANGUSTIFOLIA WHOLE; GLYCERIN; ILEX PARAGUARIENSIS LEAF; DIMETHYL SULFONE

MedFreeze Naturally Cool Pain Relief Spray

Active ingredients

Menthol 12%

Purpose

Cooling pain relief

Uses

Temporary relief of minor aches and pains of muscles and joints associated with: Simple, backache, arthritis, strains, sprains.

Warnings

- For external use only
- Flammable
- Keep away from excessive heat or open flame
- Avoid spraying in eyes
- Contents under pressure. Do not puncture or incinerate container. Do not store at temperature above 120°F (48°C)

Do not use

- With heating pad or device
- With ointments, creams, sprays or liniments
- On wounds, damaged skin or irritated skin

Ask a doctor before use if you

- Have sensitive skin
- Are pregnant or breastfeeding

When using this product

- Avoid contact with eyes or mucous membranes
- Do not bandage tightly

Stop use and ask a doctor if

- Condition worsens
- Symptoms persist for more than 7 days or clear up then reoccur again within a few days
- Irritation develops

Keep out of reach of children.

If swallowed, get medical help or contact a Poison Control Center right away.

Instructions

Adults / Children 2 years and older:

- Spray on the affected area not more than 3 to 4 times daily
- Shake well before use

Children under 2 years old:Consult a physician.

Other information

- Replace cap after use
- Store in a cool, dry place

Ingredients

Aqua (deionized water), Calendula officinalis extract, Camellia Sinensis (green tea) extract, Chamomilla Matricaria (chamomile) extract, Citric acid, Echinacea angustifolia extract, Glycerin, Ilex Paraguariensis (Yerba Mate) extract, Berry extract of Juniperus Communis (juniper), Methylsulfonylmethane (MSM), SD-Alcohol 40B.

Questions?

Call 786-956-7146